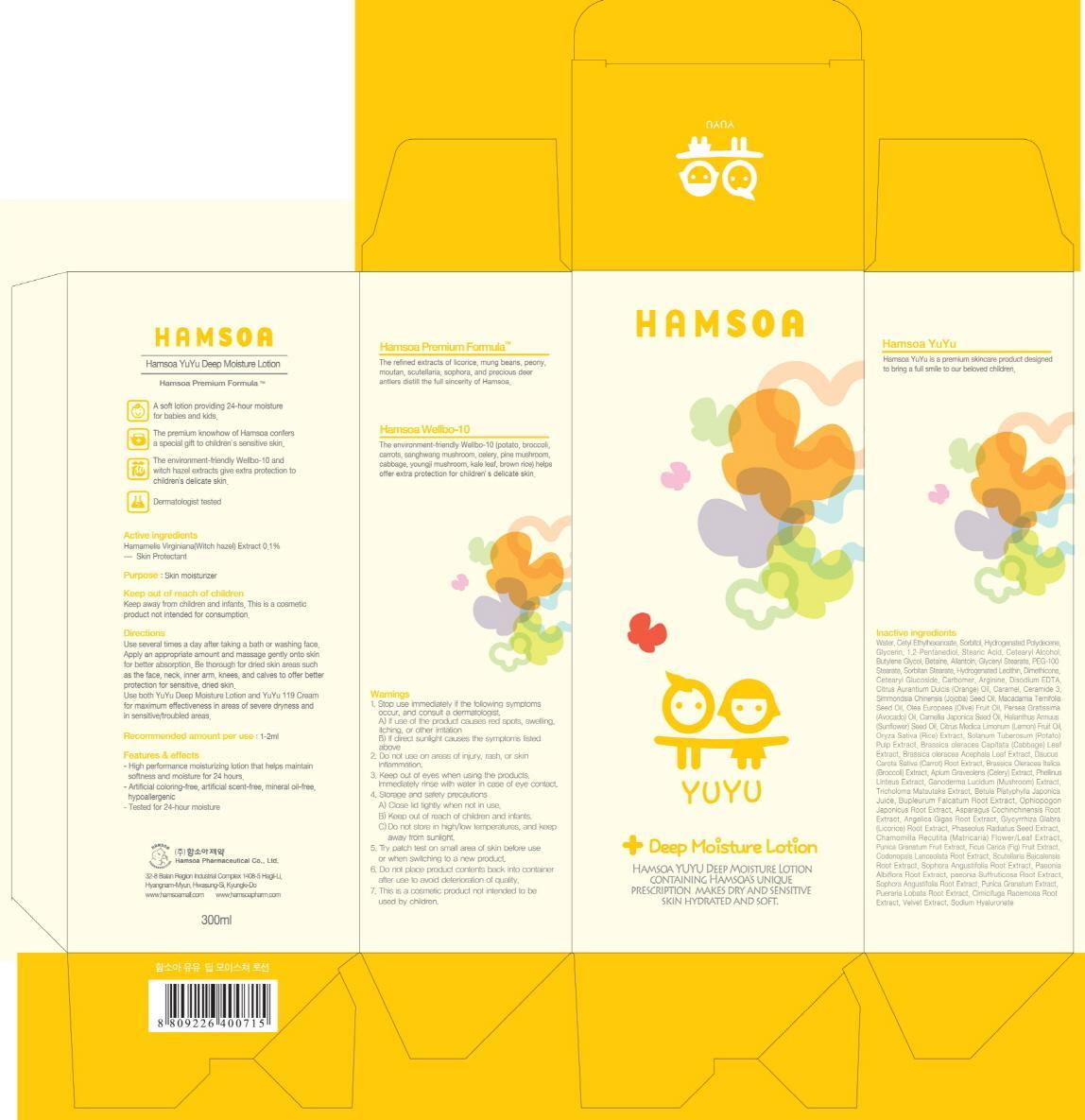 DRUG LABEL: HAMSOA YUYU DEEP MOISTURE
NDC: 50964-090 | Form: LOTION
Manufacturer: HAMSOA PHARMACEUTICAL CO., LTD.
Category: otc | Type: HUMAN OTC DRUG LABEL
Date: 20120825

ACTIVE INGREDIENTS: WITCH HAZEL 0.3 g/300 mL
INACTIVE INGREDIENTS: WATER; CETYL ETHYLHEXANOATE; SORBITOL; GLYCERIN; PENTYLENE GLYCOL; STEARIC ACID

ACTIVE INGREDIENT

Active ingredient: Witch hazel(Hamamelis Virginiana) 0.1%

INACTIVE INGREDIENT

Inactive ingredients
Water, Cetyl Ethylhexanoate, Sorbitol, Hydrogenated Polydecene, Glycerin, 1,2-Pentanediol, Stearic Acid, Cetearyl Alcohol, Butylene Glycol,
Betaine, Allantoin, Glyceryl Stearate, PEG-100 Stearate, Sorbitan Stearate, Hydrogenated Lecithin, Dimethicone, Cetearyl Glucoside, Carbomer, Arginine, Disodium EDTA, Citrus Aurantium Dulcis (Orange) Oil, Caramel, Ceramide 3, Simmondsia Chinensis (Jojoba) Seed Oil, Macadamia Ternifolia Seed Oil, Olea Europaea (Olive) Fruit Oil, Persea Gratissima (Avocado) Oil, Camellia Japonica Seed Oil, Helianthus Annuus (Sunflower) Seed Oil, Citrus Medica Limonum (Lemon) Fruit Oil, Oryza Sativa (Rice) Extract, Solanum Tuberosum (Potato) Pulp Extract, Brassica oleracea Capitata (Cabbage) Leaf Extract, Brassica oleracea Acephala Leaf Extract, Daucus Carota Sativa (Carrot) Root Extract, Brassica Oleracea Italica (Broccoli) Extract, Apium Graveolens (Celery) Extract, Phellinus Linteus Extract,
Ganoderma Lucidum (Mushroom) Extract, Tricholoma Matsutake Extract, Betula Platyphylla Japonica Juice, Bupleurum Falcatum Root Extract, Ophiopogon Japonicus Root Extract, Asparagus Cochinchinensis Root Extract, Angelica Gigas Root Extract, Glycyrrhiza Glabra (Licorice) Root Extract, Phaseolus Radiatus Seed Extract, Chamomilla Recutita (Matricaria) Flower/Leaf Extract, Punica Granatum Fruit Extract, Ficus Carica (Fig) Fruit Extract, Codonopsis Lanceolata Root Extract, Scutellaria Baicalensis Root Extract, Sophora Angustifolia Root Extract, Paeonia Albiflora Root Extract, paeonia Suffruticosa Root Extract, Sophora Angustifolia Root Extract, Punica Granatum Extract, Pueraria Lobata Root Extract, Cimicifuga Racemosa Root Extract, Velvet Extract, Sodium Hyaluronate

PURPOSE

Purpose: Skin moisturizer

WARNINGS

1. Stop use immediately if the following symptoms occur, and consult a dermatologist.
A) If use of the product causes red spots, swelling, itching, or other irritation
B) If direct sunlight causes the symptoms listed above
2. Do not use on areas of injury, rash, or skin inflammation.
3. Keep out of eyes when using the products. Immediately rinse with water in case of eye contact.
4. Storage and safety precautions
A) Close lid tightly when not in use.
B) Keep out of reach of children and infants.
C)Do not store in high/low temperatures, and keep away from sunlight.
5. Try patch test on small area of skin before use or when switching to a new product.
6. Do not place product contents back into container after use to avoid deterioration of quality.
7. This is a cosmetic product not intended to be used by children

KEEP OUT OF REACH OF CHILDREN

Keep away from children and infants.
This is a cosmetic product not intended for consumption.

INDICATIONS AND USAGE

Directions:
Use several times a day after taking a bath or washing face.
Apply an appropriate amount and massage gently onto skin for better absorption.
Be thorough for dried skin areas such as the face, neck, inner arm, knees, and calves to offer better protection for sensitive, dried skin.
Use both YuYu Deep Moisture Lotion and YuYu 119 Cream for maximum effectiveness in areas of severe dryness and in sensitive/troubled areas.

DOSAGE AND ADMINISTRATION

Recommended amount per use: 1-2g